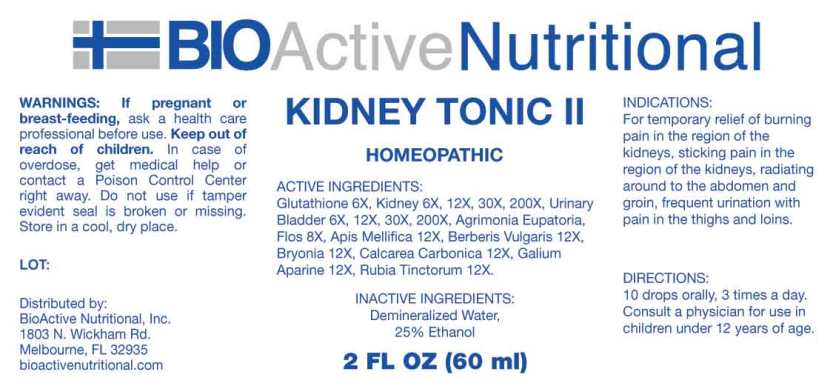 DRUG LABEL: Kidney Tonic
NDC: 43857-0579 | Form: LIQUID
Manufacturer: BioActive Nutritional, Inc.
Category: homeopathic | Type: HUMAN OTC DRUG LABEL
Date: 20240829

ACTIVE INGREDIENTS: GLUTATHIONE 6 [hp_X]/1 mL; PORK KIDNEY 6 [hp_X]/1 mL; SUS SCROFA URINARY BLADDER 6 [hp_X]/1 mL; AGRIMONIA EUPATORIA FLOWER 8 [hp_X]/1 mL; APIS MELLIFERA 12 [hp_X]/1 mL; BERBERIS VULGARIS ROOT BARK 12 [hp_X]/1 mL; BRYONIA ALBA WHOLE 12 [hp_X]/1 mL; OYSTER SHELL CALCIUM CARBONATE, CRUDE 12 [hp_X]/1 mL; GALIUM APARINE WHOLE 12 [hp_X]/1 mL; RUBIA TINCTORUM ROOT 12 [hp_X]/1 mL
INACTIVE INGREDIENTS: WATER; ALCOHOL

DRUG FACTS:

ACTIVE INGREDIENTS:

Glutathione 6X, Kidney 6X, 12X, 30X, 200X, Urinary Bladder (Suis) 6X, 12X, 30X, 200X, Agrimonia Eupatoria, Flos 8X, Apis Mellifica 12X, Berberis Vulgaris 12X, Bryonia (Alba) 12X, Calcarea Carbonica 12X, Galium Aparine 12X, Rubia Tinctorum 12X.

INDICATIONS:

For temporary relief of burning pain in the region of the kidneys, sticking pain in the region of the kidneys, radiatingaround the abdomen and groin, frequent urination with painin the thighs and loins.

WARNINGS:

If pregnant or breast-feeding, ask a health care professional before use.

Keep out of reach of children. In case of overdose, get medical help or contact a Poison Control Center right away.

Do not use if tamper evident seal is broken or missing.

Store in cool, dry place.

Keep out of reach of children. In case of overdose, get medical help or contact a Poison Control Center right away.

DIRECTIONS:

10 drops orally, 3 times a day. Consult a physician for use in children under 12 years of age.

INDICATIONS:

For temporary relief of burning pain in the region of the kidneys, sticking pain in the region of the kidneys, radiatingaround the abdomen and groin, frequent urination with painin the thighs and loins.

INACTIVE INGREDIENTS:

Demineralized Water, 25% Ethanol

QUESTIONS:

Distributed by:
BioActive Nutritional, Inc.
1803 N. Wickham Rd.
Melbourne, FL 32935
bioactivenutritional.com

PACKAGE LABEL DISPLAY:

BIOActive Nutritional

KIDNEY TONIC II

HOMEOPATHIC

2 FL OZ (60 ml)